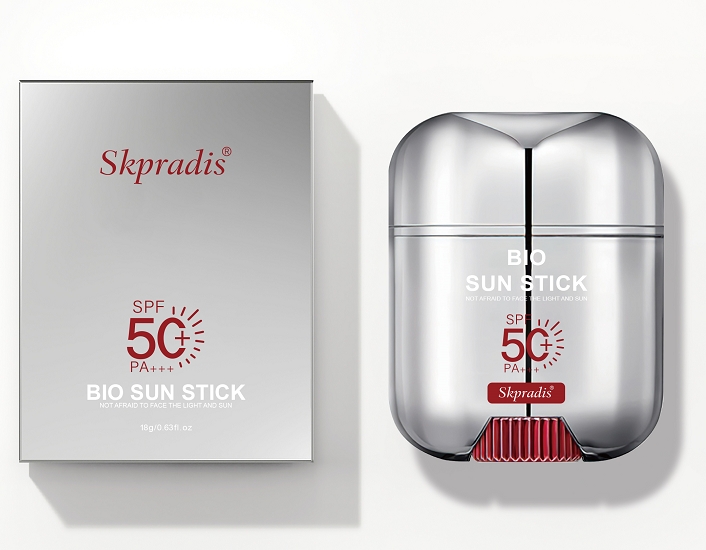 DRUG LABEL: Skpradis Sunscreen Stick
NDC: 84507-036 | Form: STICK
Manufacturer: Guangdong Miaolian Cosmetics Co., Ltd.
Category: otc | Type: HUMAN OTC DRUG LABEL
Date: 20250331

ACTIVE INGREDIENTS: .ALPHA.-TOCOPHEROL 0.438 mg/100 g
INACTIVE INGREDIENTS: TRIDECYL TRIMELLITATE; ETHYLHEXYL PALMITATE; ETHYLHEXYL METHOXYCINNAMATE; OCTOCRYLENE; VINYL DIMETHICONE/METHICONE SILSESQUIOXANE CROSSPOLYMER; ALOE BARBADENSIS LEAF; CAPRYLYL GLYCOL; NIACINAMIDE; CERESIN; SYNTHETIC WAX (540 MW); BIS-ETHYLHEXYLOXYPHENOL METHOXYPHENYL TRIAZINE; ACETYL HEXAPEPTIDE-8; CAPRYLIC/CAPRIC TRIGLYCERIDE; DIETHYLHEXYL BUTAMIDO TRIAZONE; CI 19140; ETHYLHEXYL SALICYLATE; WATER; PHENOXYETHANOL; COPPER TRIPEPTIDE-1; DICAPRYLYL CARBONATE; ISODODECANE; SILICA DIMETHYL SILYLATE; BHT; FRAGRANCE LEMON ORC2001060; MICROCRYSTALLINE WAX; BUTYLENE GLYCOL

PURPOSE

Sunscreen

WARNINGS

For external use only

ACTIVE INGREDIENT

TOCOPHERYL ACETATE -----0.438%

Keep out of reach of children. lf swallowed, get medical help orcontact Poison Control Center right away

DOSAGE AND ADMINISTRATION

Apply liberally/generously (and evenly) 15 minutes before sun exposure
For use on children less than 6 months of age, consult a health care practitioner
Reapply
At least every 2 hours
After 80 minutes of swimming or sweating
Immediately after towel drying

INDICATIONS AND USAGE

Helps prevent sunbum.
lf used as directed with other sun protectionmeasures (see Directions), decreases the risk of skin cancer and early skin aging caused by the sun.

INACTIVE INGREDIENT

ETHYLHEXYL PALMITATE
MICROCRYSTALLINE WAX
CAPRYLIC/CAPRIC TRIGLYCERIDE
OZOKERITE
ETHYLHEXYL SALICYLATE
SYNTHETIC WAX
DICAPRYLYL CARBONATE
DIETHYLHEXYL BUTAMIDO TRIAZONE
BIS-ETHYLHEXYLOXYPHENOL METHOXYPHENYL TRIAZINE
ISODODECANE
ETHYLHEXYL METHOXYCINNAMATE
BHT
OCTOCRYLENE
Vinyl Dimethicone/Methicone Silsesquioxane Crosspolymer
SILICA DIMETHYL SILYLATE
FRAGRANCE
TRIDECYL TRIMELLITATE
CI 19140
WATER
BUTYLENE GLYCOL
ALOE BARBADENSIS LEAF EXTRACT
PHENOXYETHANOL
WATER
CAPRYLYL GLYCOL
ACETYL HEXAPEPTIDE-8
COPPER TRIPEPTIDE-1
NIACINAMIDE